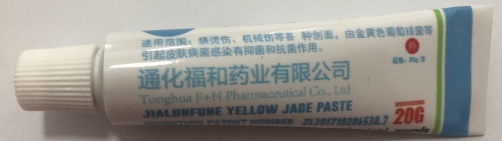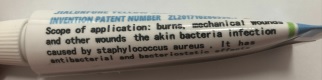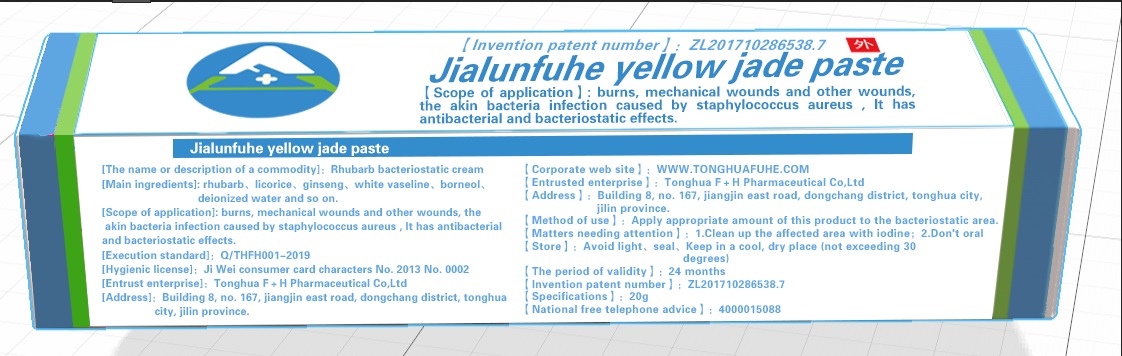 DRUG LABEL: Rhubarb bacteriostatic cream
NDC: 75251-001 | Form: PASTE
Manufacturer: Tonghua fuhe Pharmaceutical Co,Ltd
Category: otc | Type: HUMAN OTC DRUG LABEL
Date: 20200415

ACTIVE INGREDIENTS: ASIAN GINSENG 5 g/20 g; LICORICE 2 g/20 g; RHUBARB 1 g/20 g
INACTIVE INGREDIENTS: PETROLATUM; BORNEOL; WATER

Rhubarb bacteriostatic cream

Rhubarb bacteriostatic cream

Active Ingredient(s)

rhubarb 1g/20g
icorice 2g/20g
ginseng 5g/20g

Purpose

Scope of application: burns, mechanical wounds and other wounds, the skin bacteria infection caused by staphylococcus aureus. It has antibacterial and bacteriostatic effects.

Use

Scope of application: burns, mechanical wounds and other wounds, the skin bacteria infection caused by staphylococcus aureus. It has antibacterial and bacteriostatic effects.

Warnings

For external use only. Flammable. Keep away from heat or flame

Do not use

- in children less than 2 months of age

When using this product keep out of eyes, ears, and mouth. In case of contact with eyes, rinse eyes thoroughly with water.
Stop use and ask a doctor if irritation or rash occurs. These may be signs of a serious condition.
Keep out of reach of children. If swallowed, get medical help or contact a Poison Control Center right away.

Stop use and ask a doctor if irritation or rash occurs. These may be signs of a serious condition.

Keep out of reach of children. If swallowed, get medical help or contact a Poison Control Center right away.

Directions

- Clean up the affected area with iodine.
- Apply appropriate amount of this product to the bacteriostatic area.
- Supervise children under 6 years of age when using this product to avoid swallowing.

Other information

- Store between 15-30C (59-86F)
- Avoid freezing and excessive heat above 40C (104F)
- Avoid light, seal, keep in a cool, dry place.
- The period of validity: 24 months.

Inactive ingredients

vaseline
borneol
deionized water

Package Label - Principal Display Panel

20 g NDC: 75251-001-01